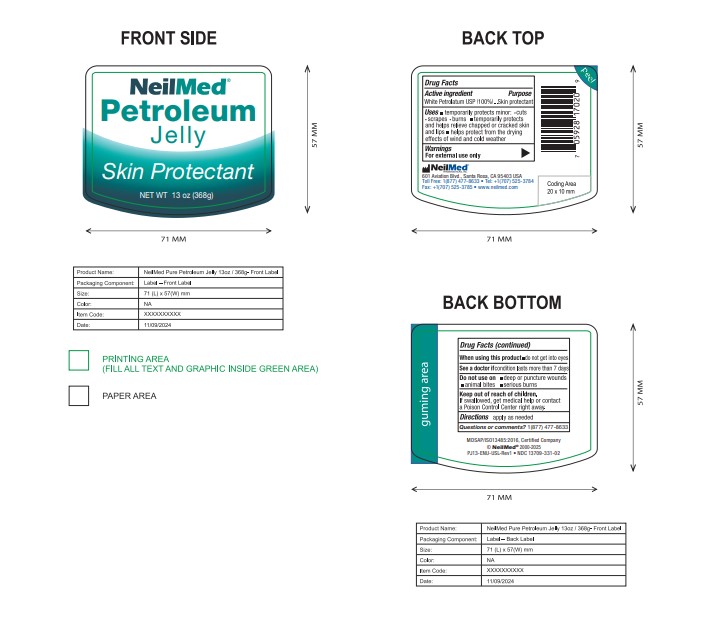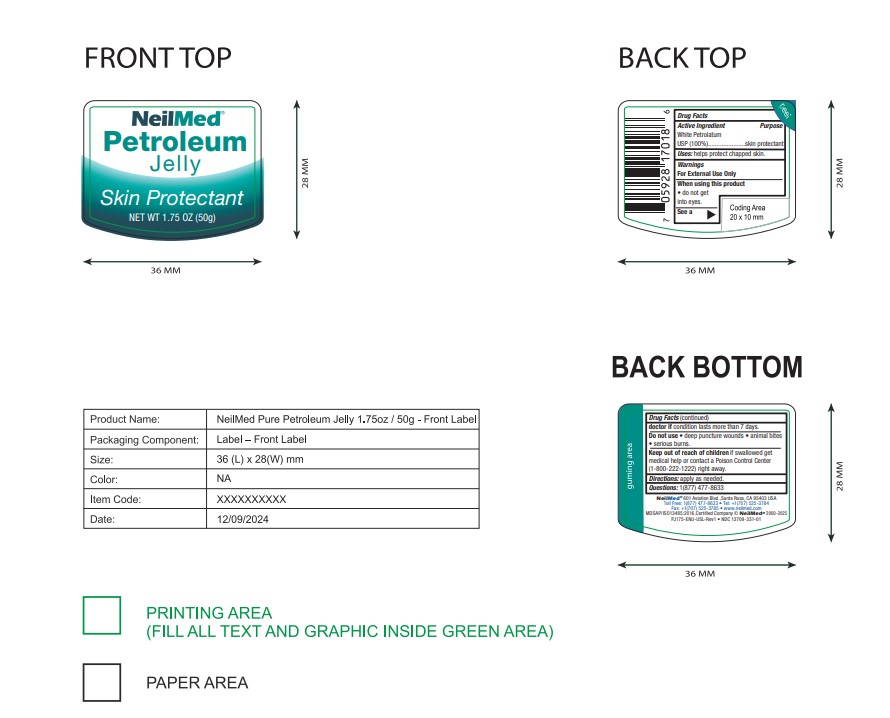 DRUG LABEL: Petroleum Jelly
NDC: 13709-331 | Form: JELLY
Manufacturer: NeilMed Pharmaceuticals Inc.
Category: otc | Type: HUMAN OTC DRUG LABEL
Date: 20250721

ACTIVE INGREDIENTS: WHITE PETROLATUM 100 g/100 g

Petroleum Jelly Skin Protectant

Active Ingredient

White Petrolatum USP (100%)

Purpose

White Petrolatum USP (100%).......Skin protectant

Uses

- temporarily protects minor: cuts scrapes burns
- temporarily protects and helps relieve chapped or cracked skin and lips
- helps protect from the drying effects of wind and cold weather

Warnings

For external use only

When using this product

- do not get into eyes

See a doctor if

condition lasts more than 7 days

Do not use on

- deep or puncture wounds
- animal bites
- serious burns

Keep out of reach of children.

If swallowed, get medical help or contact a Poison Control Center right away.

Directions

apply as needed

Questions or comments?

1(877)477-8633

Inactive Ingredients

White Petrolatum